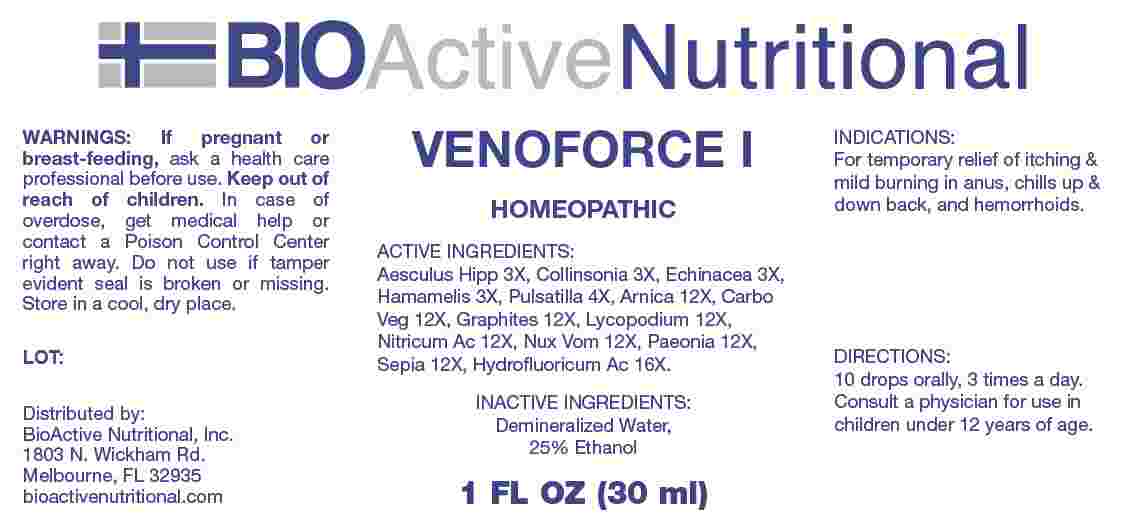 DRUG LABEL: Venoforce
NDC: 43857-0651 | Form: LIQUID
Manufacturer: BioActive Nutritional, Inc.
Category: homeopathic | Type: HUMAN OTC DRUG LABEL
Date: 20250106

ACTIVE INGREDIENTS: HORSE CHESTNUT 3 [hp_X]/1 mL; COLLINSONIA CANADENSIS ROOT 3 [hp_X]/1 mL; ECHINACEA ANGUSTIFOLIA WHOLE 3 [hp_X]/1 mL; HAMAMELIS VIRGINIANA ROOT BARK/STEM BARK 3 [hp_X]/1 mL; PULSATILLA VULGARIS WHOLE 4 [hp_X]/1 mL; ARNICA MONTANA WHOLE 12 [hp_X]/1 mL; ACTIVATED CHARCOAL 12 [hp_X]/1 mL; GRAPHITE 12 [hp_X]/1 mL; LYCOPODIUM CLAVATUM SPORE 12 [hp_X]/1 mL; NITRIC ACID 12 [hp_X]/1 mL; STRYCHNOS NUX-VOMICA SEED 12 [hp_X]/1 mL; PAEONIA OFFICINALIS ROOT 12 [hp_X]/1 mL; SEPIA OFFICINALIS JUICE 12 [hp_X]/1 mL; HYDROFLUORIC ACID 16 [hp_X]/1 mL
INACTIVE INGREDIENTS: WATER; ALCOHOL

DRUG FACTS:

ACTIVE INGREDIENTS:

Aesculus Hippocastanum 3X, Collinsonia Canadensis 3X, Echinacea 3X, Hamamelis Virginiana 3X, Pulsatilla 4X, Arnica Montana 12X, Carbo Vegetabilis 12X, Graphites 12X, Lycopodium Clavatum 12X, Nitricum Acidum 12X, Nux Vomica 12X, Paeonia Officinalis 12X, Sepia 12X, Hydrofluoricum Acidum 16X.

PURPOSE:

For temporary relief of itching & mild burning in anus, chills up & down back, and hemorrhoids.

WARNINGS:

If pregnant or breast-feeding, ask a health care professional before use.

Keep out of reach of children. In case of overdose, get medical help or contact a Poison Control Center right away.

Do not use if tamper evident seal is broken or missing.

Store in a cool, dry place.

KEEP OUT OF REACH OF CHILDREN:

In case of overdose, get medical help or contact a Poison Control Center right away.

DIRECTIONS:

10 drops orally, 3 times a day. Consult a physician for use in children under 12 years of age.

INDICATIONS:

For temporary relief of itching & mild burning in anus, chills up & down back, and hemorrhoids.

INACTIVE INGREDIENTS:

Demineralized Water, 25% Ethanol

QUESTIONS:

Distributed by:
BioActive Nutritional, Inc.
1803 N. Wickham Rd.
Melbourne, FL 32935
bioactivenutritional.com

PACKAGE LABEL DISPLAY:

BIOActiveNutritional

VENOFORCE I

HOMEOPATHIC

1 FL OZ (30 ml)